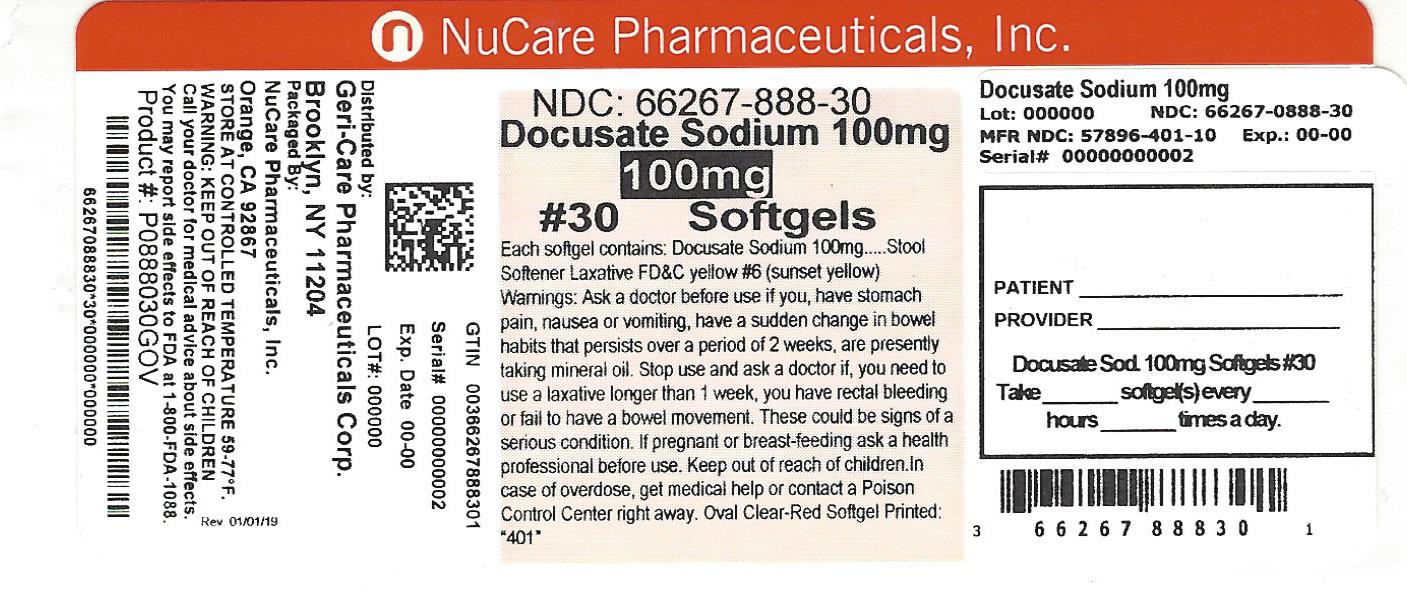 DRUG LABEL: Docusate Sodium
NDC: 66267-888 | Form: CAPSULE, LIQUID FILLED
Manufacturer: NuCare Pharmaceuticals,Inc.
Category: otc | Type: HUMAN OTC DRUG LABEL
Date: 20240814

ACTIVE INGREDIENTS: DOCUSATE SODIUM 100 mg/1 1
INACTIVE INGREDIENTS: GELATIN; GLYCERIN; POLYETHYLENE GLYCOL 400; PROPYLENE GLYCOL; SORBITOL; WATER; D&C YELLOW NO. 10; FD&C YELLOW NO. 6; FD&C RED NO. 40; MANNITOL

Active ingredient (in each softgel)

Docusate Sodium 100 mg

Purpose

Stool Softener Laxative

Uses

- relieves occasional constipation (irregularity)

- generally produces bowel movement in 12 to 72 hours

Warnings

Ask a doctor before use if you

• have stomach pain, nausea or vomiting

• have a sudden change in bowel habits that persists over a period of 2 weeks

• are presently taking mineral oil

Stop use and ask a doctor if

• you need to use a laxative longer than 1 week

• you have rectal bleeding or fail to have a bowel movement. These

could be signs of a serious condition.

If pregnant or breast-feeding, ask a health professional before use.

Keep out of reach of children. In case of overdose, get medical help or contact a Poison Control Center right away.

Directions

• adults and children 12 years and older: take 1-2 softgel daily until first bowel movement; 1 softgel daily thereafter, or as directed by doctor

• children under 12: consult a doctor

• do not exceed recommended dose

Other information

• each softgel contains: sodium 5 mg. very low sodium

• store at 15°C-25°C(59° F-77° F)

• keep tightly closed

• product from USA or Canada

• Tamper Evident: Do not use if imprinted seal under cap is missing or broken.

Inactive ingredients

FD and C red 40, gelatin, glycerin, edible ink, PEG, propylene glycol, sorbitol special, water. May also contain D and C yellow 10, FD and C yellow 6 (sunset yellow), mannitol.